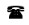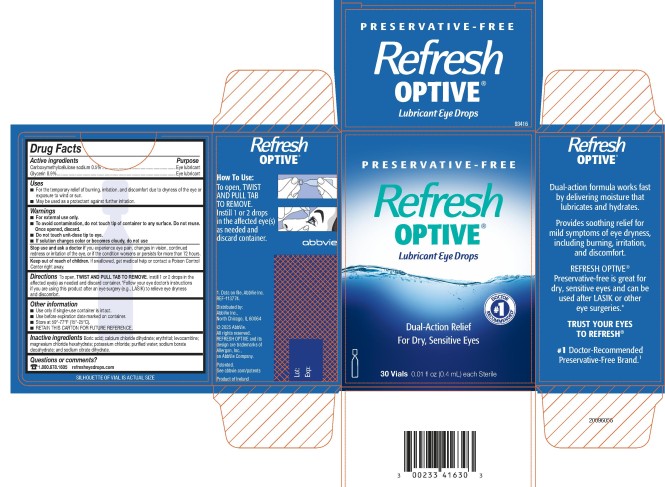 DRUG LABEL: Refresh Optive
NDC: 0023-3416 | Form: SOLUTION/ DROPS
Manufacturer: Allergan, Inc.
Category: otc | Type: HUMAN OTC DRUG LABEL
Date: 20250822

ACTIVE INGREDIENTS: Carboxymethylcellulose Sodium 5 mg/1 mL; Glycerin 9 mg/1 mL
INACTIVE INGREDIENTS: Boric Acid; Calcium Chloride; Erythritol; Levocarnitine; Magnesium Chloride; potassium chloride; water; sodium borate; trisodium citrate dihydrate

REFRESH OPTIVE®
Drug Facts

Active ingredients

Carboxymethylcellulose sodium 0.5%

Glycerin 0.9%

Purpose

Eye lubricant

Eye lubricant

Uses

- For the temporary relief of burning, irritation, and discomfort due to dryness of the eye or exposure to wind or sun.
- May be used as a protectant against further irritation.

Warnings

- For external use only.
- To avoid contamination, do not touch tip of container to any surface. Do not reuse. Once opened, discard.
- Do not touch unit-dose tip to eye.
- If solution changes color or becomes cloudy, do not use.

Stop use and ask a doctor if

you experience eye pain, changes in vision, continued redness or irritation of the eye, or if the condition worsens or persists for more than 72 hours.

Keep out of reach of children.

If swallowed, get medical help or contact a Poison Control Center right away.

Directions

To open, TWIST AND PULL TAB TO REMOVE. Instill 1 or 2 drops in the affected eye(s) as needed and discard container. *Follow your eye doctor’s instructions if you are using this product after an eye surgery (e.g., LASIK) to relieve eye dryness and discomfort.

Other information

- Use only if single-use container is intact.
- Use before expiration date marked on container.
- Store at 59°-77°F (15°-25°C).
- RETAIN THIS CARTON FOR FUTURE REFERENCE.

Inactive ingredients

Boric acid; calcium chloride dihydrate; erythritol; levocarnitine; magnesium chloride hexahydrate; potassium chloride; purified water; sodium borate decahydrate; and sodium citrate dihydrate.

Questions or comments?

1.800.678.1605

refresheyedrops.com

v2.0DFL3416

PRINCIPAL DISPLAY PANEL

NDC 0023-3416-30
Preservative-free
Refresh
Optive®
Lubricant Eye Drops
Dual-Action Relief
For Dry, Sensitive Eyes
30 Vials 0.01 fl oz (0.4 mL) each Sterile